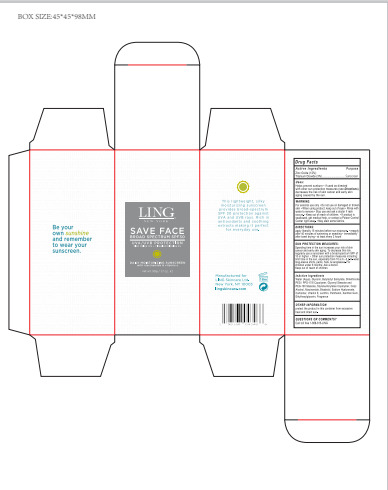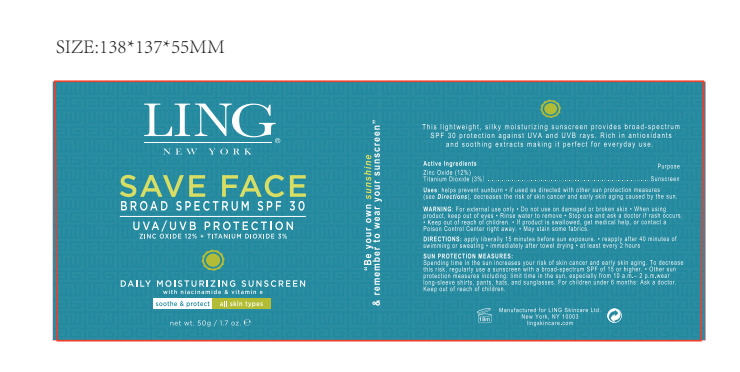 DRUG LABEL: LING NEW YORK Save Face Broad Spectrum SPF 30
NDC: 83447-008 | Form: CREAM
Manufacturer: Guangzhou Fantesy Biotechnology Co.,Ltd
Category: otc | Type: HUMAN OTC DRUG LABEL
Date: 20260105

ACTIVE INGREDIENTS: TITANIUM DIOXIDE 3 g/100 g; ZINC OXIDE 12 g/100 g
INACTIVE INGREDIENTS: WATER; GLYCERIN; BUTYLOCTYL SALICYLATE; HYALURONATE SODIUM; DIMETHICONE; GLYCERYL MONOSTEARATE; ETHYLHEXYLGLYCERIN; PEG-100 STEARATE; XANTHAN GUM; PHOSPHATIDYLCHOLINE, SOYBEAN; PEG/PPG-17/6 COPOLYMER; PREGNENOLONE; PANTHENOL; CETYL ALCOHOL; NIACINAMIDE; .ALPHA.-BISABOLOL, (+)-; TOCOPHEROL

83447-008

ACTIVE INGREDIENT

Zinc Oxide 12%

Titanium Dioxide 3%

PURPOSE

sunscreen

Uses

■helps prevent sunburn
■if used as directed with other sun protection measures (see Directions), decreases the risk of skin cancer and early
skin aging caused by the sun

Warnings

①For external use only. ②Do not use on damaged or broken skin. ③When using this product keep out of eyes. Rinse with water to remove. ④Stop use and ask a doctor if rash occurs. ⑤Keep out of reach of children. If product is swallowed, get medical help or contact a Poison Control Center right away. ⑥ May stain some fabrics.

Do not use on damaged or broken skin.

Keep out of reach of children. If product is swallowed, get medical help or contact a Poison Control Center right away.

Directions

apply liberally 15 minutes before sun exposure.●reapply after 40 minutes of swimming or sweating●immediately
after towel drying ●at least every 2 hours

Other information

protect the product in this container from excessive heat and direct sun.

Inactive Ingredients

Water (Aqua)」Glycerin, Butyloctyl Salicylate, Dimethicone PEG I PPG-17/6 Copolymer, Glyceryl Stearate and
PEG-100 Stearate, Styrene/Acrylates Copolymer, Cetyl Alcohol, Niacinamide, Bisabolol, Sodium Hyaluronate,
Carbomer, Vitamin E, Lecithin, Panthenol, Xanthan Gum, Ethylhexylglycerin, Fragrance